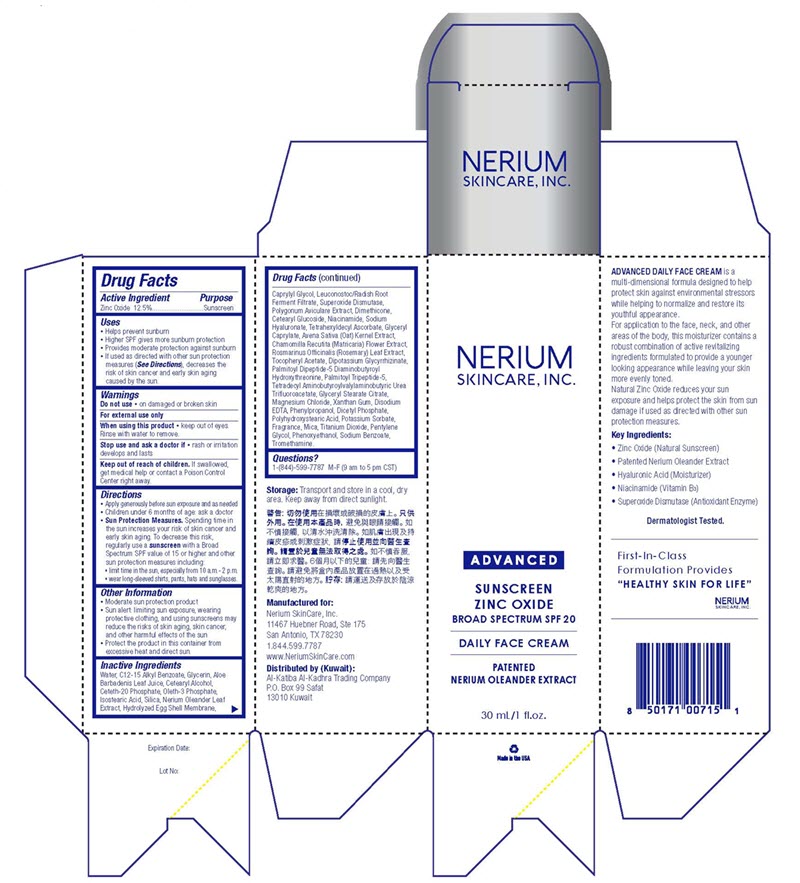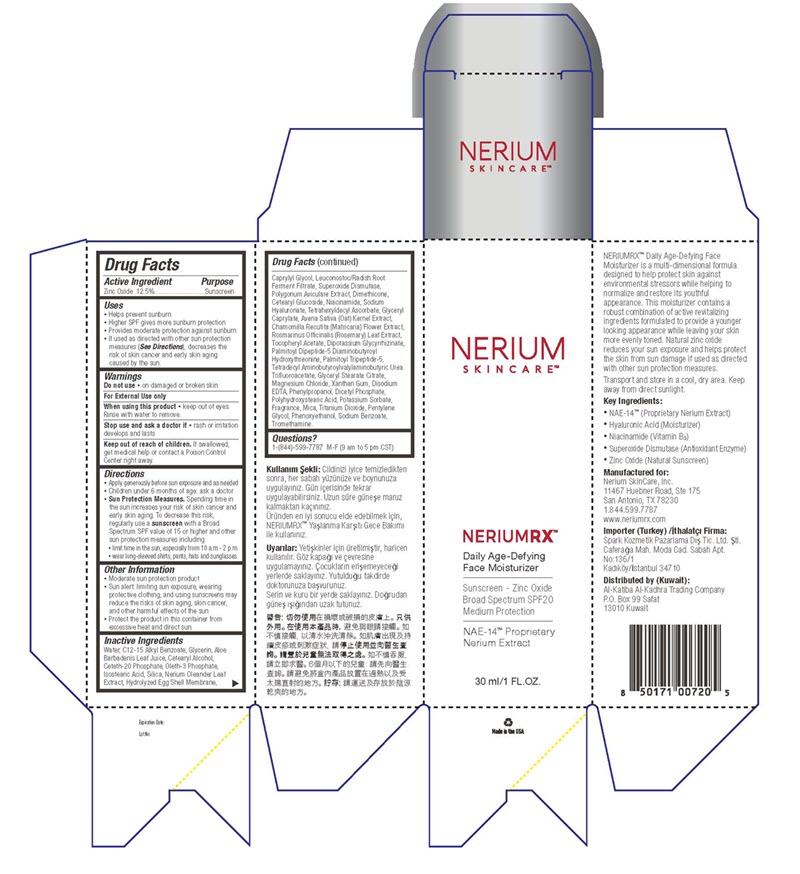 DRUG LABEL: Daily SPF 20 Oleander Face Cream
NDC: 10477-0063 | Form: CREAM
Manufacturer: Goodier Cosmetics
Category: otc | Type: HUMAN OTC DRUG LABEL
Date: 20211019

ACTIVE INGREDIENTS: ZINC OXIDE 12.5 g/100 g
INACTIVE INGREDIENTS: WATER; ALKYL (C12-15) BENZOATE; GLYCERIN; ALOE VERA LEAF; CETETH-20 PHOSPHATE; OLETH-3 PHOSPHATE; ISOSTEARIC ACID

Daily SPF 20 Oleander Face Cream

NeriumRX™ Daily Age-Defying Face Moisturizer

NERIUM
SKINCARE™

NeriumRX™
Daily Age-Defying
Face Moisturizer

Sunscreen - Zinc Oxide
Broad Spectrum SPF20
Medium Protection

NAE-14™ Proprietary
Nerium Extract

30 ml/1 FL.OZ.

Active Ingredient Purpose
Zinc Oxide 12.5%............................Sunscreen

Uses
• Helps prevent sunburn
• Higher SPF gives more sunburn protection
• Provides moderate protection against sunburn
• If used as directed with other sun protection
measures (See Directions), decreases the
risk of skin cancer and early skin aging
caused by the sun.

Warnings

Do not use • on damaged or broken skin

WHEN USING

For External Use only
When using this product • keep out of eyes.
Rinse with water to remove.

Stop use and ask a doctor if • rash or irritation develops and lasts

Keep out of reach of children. If swallowed, get medical help or contact a Poison Control
Center right away.

Directions
• Apply generously before sun exposure and as needed
• Children under 6 months of age: ask a doctor
• Sun Protection Measures. Spending time in the sun increases your risk of skin cancer and
early skin aging. To decrease this risk, regularly use a sunscreen with a Broad
Spectrum SPF value of 15 or higher and other sun protection measures including:
• limit time in the sun, especially from 10 a.m.- 2 p.m.
• wear long-sleeved shirts, pants, hats and sunglasses.

Other Information
• Moderate sun protection product
• Sun alert: limiting sun exposure, wearing protective clothing, and using sunscreens may
reduce the risks of skin aging, skin cancer, and other harmful effects of the sun
• Protect the product in this container from excessive heat and direct sun.

Inactive Ingredients
Water, C12-15 Alkyl Benzoate, Glycerin, Aloe Barbadenis Leaf Juice, Cetearyl Alcohol,
Ceteth-20 Phosphate, Oleth-3 Phosphate, Isostearic Acid, Silica, Nerium Oleander Leaf
Extract, Hydrolyzed Egg Shell Membrane, Caprylyl Glycol, Leuconostoc/Radish Root
Ferment Filtrate, Superoxide Dismutase, Polygonum Aviculare Extract, Dimethicone,
Cetearyl Glucoside, Niacinamide, Sodium Hyaluronate, Tetrahexyldecyl Ascorbate, Glyceryl
Caprylate, Avena Sativa (Oat) Kernel Extract, Chamomilla Recutita (Matricaria) Flower Extract,
Rosmarinus Officinalis (Rosemary) Leaf Extract, Tocopheryl Acetate, Dipotassium Glycyrrhizinate,
Palmitoyl Dipeptide-5 Diaminobutyroyl Hydroxythreonine, Palmitoyl Tripeptide-5,
Tetradecyl Aminobutyroylvalylaminobutyric Urea Trifluoroacetate, Glyceryl Stearate Citrate,
Magnesium Chloride, Xanthan Gum, Disodium EDTA, Phenylpropanol, Dicetyl Phosphate,
Polyhydroxystearic Acid, Potassium Sorbate, Fragrance, Mica, Titanium Dioxide, Pentylene
Glycol, Phenoxyethanol, Sodium Benzoate, Tromethamine.

Manufactured for:
Nerium SkinCare, Inc.
11467 Huebner Road, Ste 175
San Antonio, TX 78230

Nerium Advanced Daily Face Cream

NERIUM
SKINCARE, INC.

ADVANCED

SUNSCREEN
ZINC OXIDE
BROAD SPECTRUM SPF 20

DAILY FACE CREAM

PATENTED
NERIUM OLEANDER EXTRACT

30 mL/1 fl.oz.

Active Ingredient Purpose
Zinc Oxide 12.5%............................Sunscreen

Uses
• Helps prevent sunburn
• Higher SPF gives more sunburn protection
• Provides moderate protection against sunburn
• If used as directed with other sun protection measures (See Directions), decreases the
risk of skin cancer and early skin aging caused by the sun.

Warnings

Do not use • on damaged or broken skin

WHEN USING

For External Use only
When using this product • keep out of eyes. Rinse with water to remove.

Stop use and ask a doctor if • rash or irritation develops and lasts

Keep out of reach of children. If swallowed, get medical help or contact a Poison Control
Center right away.

Directions
• Apply generously before sun exposure and as needed
• Children under 6 months of age: ask a doctor
• Sun Protection Measures. Spending time in the sun increases your risk of skin cancer and
early skin aging. To decrease this risk, regularly use a sunscreen with a Broad
Spectrum SPF value of 15 or higher and other sun protection measures including:
• limit time in the sun, especially from 10 a.m.- 2 p.m.
• wear long-sleeved shirts, pants, hats and sunglasses.

Other Information
• Moderate sun protection product
• Sun alert: limiting sun exposure, wearing protective clothing, and using sunscreens may
reduce the risks of skin aging, skin cancer, and other harmful effects of the sun
• Protect the product in this container from
excessive heat and direct sun.

Inactive Ingredients
Water, C12-15 Alkyl Benzoate, Glycerin, Aloe Barbadenis Leaf Juice, Cetearyl Alcohol,
Ceteth-20 Phosphate, Oleth-3 Phosphate, Isostearic Acid, Silica, Nerium Oleander Leaf
Extract, Hydrolyzed Egg Shell Membrane, Caprylyl Glycol, Leuconostoc/Radish Root
Ferment Filtrate, Superoxide Dismutase, Polygonum Aviculare Extract, Dimethicone,
Cetearyl Glucoside, Niacinamide, Sodium Hyaluronate, Tetrahexyldecyl Ascorbate, Glyceryl
Caprylate, Avena Sativa (Oat) Kernel Extract, Chamomilla Recutita (Matricaria) Flower Extract,
Rosmarinus Officinalis (Rosemary) Leaf Extract, Tocopheryl Acetate, Dipotassium Glycyrrhizinate,
Palmitoyl Dipeptide-5 Diaminobutyroyl Hydroxythreonine, Palmitoyl Tripeptide-5,
Tetradecyl Aminobutyroylvalylaminobutyric Urea Trifluoroacetate, Glyceryl Stearate Citrate,
Magnesium Chloride, Xanthan Gum, Disodium EDTA, Phenylpropanol, Dicetyl Phosphate,
Polyhydroxystearic Acid, Potassium Sorbate, Fragrance, Mica, Titanium Dioxide, Pentylene
Glycol, Phenoxyethanol, Sodium Benzoate, Tromethamine.

Manufactured for:
Nerium SkinCare, Inc.
11467 Huebner Road, Ste 175
San Antonio, TX 78230

Nerium RX Label 30mL

Nerium Advanced Label 30mL